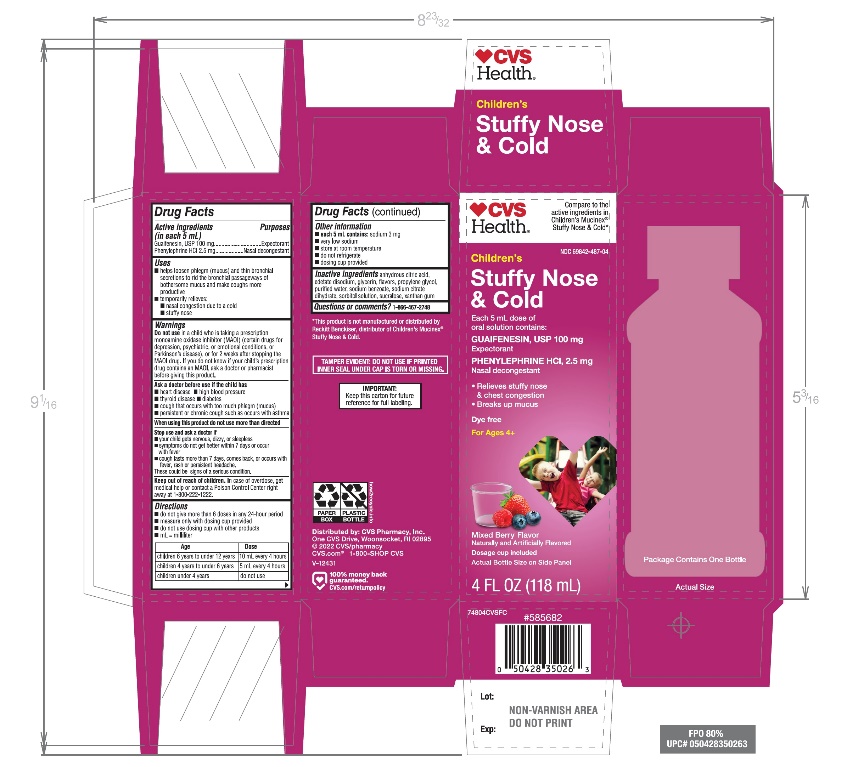 DRUG LABEL: CVS
NDC: 69842-487 | Form: SOLUTION
Manufacturer: CVS PHARMACY, INC
Category: otc | Type: HUMAN OTC DRUG LABEL
Date: 20251210

ACTIVE INGREDIENTS: GUAIFENESIN 100 mg/5 mL; PHENYLEPHRINE HYDROCHLORIDE 2.5 mg/5 mL
INACTIVE INGREDIENTS: ANHYDROUS CITRIC ACID; EDETATE DISODIUM; GLYCERIN; PROPYLENE GLYCOL; WATER; SODIUM BENZOATE; SODIUM CITRATE, UNSPECIFIED FORM; SORBITOL; SUCRALOSE; XANTHAN GUM

CVS Children's Stuffy Nose and Cold

Drug Facts

Active ingredients (in each 5 mL)

Guaifenesin, USP 100 mg

Phenylephrine HCl, 2.5 mg

Purposes

Expectorant
Nasal Decongestant

Uses

- helps loosen phlegm (mucus) and thin bronchial secretions to rid the bronchial passageways of bothersome mucus and make coughs more productive
- temporarily relieves:
  - nasal congestion due to a cold
  - stuffy nose

Warnings

Do not usein a child who is taking a prescription monoamine oxidase inhibitor (MAOI) (certain drugs for depression, psychiatric or emotional conditions, or Parkinson’s disease), or for 2 weeks after stopping the MAOI drug. If you do not know if your child’s prescription drug contains an MAOI, ask a doctor or pharmacist before giving this product.

Ask a doctor before use if the child has

- heart disease
- high blood pressure
- thyroid disease
- diabetes
- cough that occurs with too much phlegm (mucus)
- persistent or chronic cough such as occurs with asthma

When using this product

- Do not use more than directed

Stop use and ask a doctor if

- your child gets nervous, dizzy or sleepless
- symptoms do not get better within 7 days or occur with fever
- cough lasts more than 7 days, comes back, or occurs with fever, rash, or persistent headache.

These could be signs of a serious illness.

Keep out of reach of children.

In case of overdose, get medical help or contact a Poison Control Center right away (1-800-222-1222).

Directions

- do not give more than 6 doses in any 24 hour period
- measure only with dosing cup provided
- do not use dosing cup with other products
- mL= milliliter

Age | Dose
Children 6 years to under 12 years | 10 mL every 4 hours
Children 4 years to under 6 years | 5 mL every 4 hours
Children under 4 years | do not use

Other information

- each 5 mL contains: sodium 3 mg
- very low sodium
- store at room temperature
- do not refrigerate
- dosing cup provided

Inactive ingredients

anhydrous citric acid, edetate disodium, flavors, glycerin, propylene glycol, purified water, sodium benzoate, sodium citrate, sorbitol solution, sucralose, xanthan gum.

Questions or Comments?

1-866-467-2748

Package Label-Principal Display Panel 4 FL OZ (118 mL Bottle)

Compare to the Active Ingredients in Children’s Mucinex® Stuffy Nose & Cold
NDC 69842-487-04

Children's Stuffy Nose & Cold Relief

Guaifenesin

Expectorant

Phenylephrine Hcl

Nasal Decongestant

- Stuffy Nose
- Chest Congestion
- Breaks Up Mucus

Dosage Cup Included

For Ages 4 & Over

Dye Free
Mixed Berry Flavor

Naturally and Artificially Flavored

4 FL OZ (118 mL)

TAMPER-EVIDENT: DO NOT USE IF PRINTED INNER SEAL UNDER CAP IS TORN OR MISSING

IMPORTANT: Keep this carton for future reference on full labeling.

Distributed by: